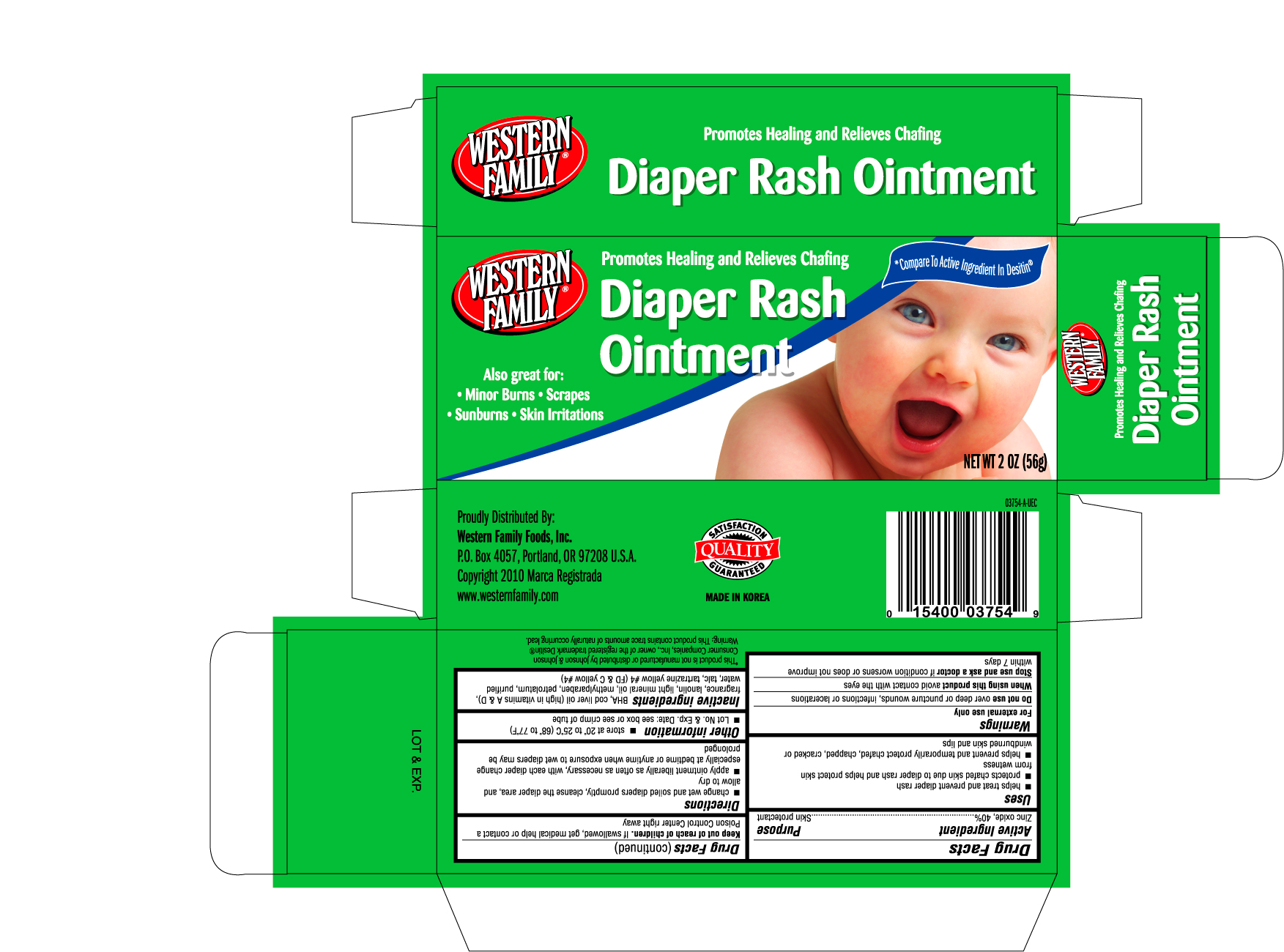 DRUG LABEL: WESTERN FAMILY DIAPER RASH
NDC: 68169-0375 | Form: OINTMENT
Manufacturer: TAI GUK PHARM. CO., LTD.
Category: otc | Type: HUMAN OTC DRUG LABEL
Date: 20101005

ACTIVE INGREDIENTS: ZINC OXIDE 0.40 g/1 g
INACTIVE INGREDIENTS: COD LIVER OIL; LANOLIN; LIGHT MINERAL OIL; METHYLPARABEN; PETROLATUM; WATER; TALC

Drug Facts

Active Ingredient Purpose

Zinc oxide, 40% ........................................................................Skin protectant

Uses

- helps treat and prevent diaper rash
- protects chafed skin due to diaper rash and helps protect skin from wetness
- helps prevent and temporarily protect chafed, chapped, cracked or windburned skin and lips

WARNINGS

For external use only

Do not use over deep or puncture wounds, infections or lacerations

When using this product avoid contact with the eyes

Stop use and ask a doctor if condition worsens or does not improve within 7 days

Keep out of reach of children. If swallowed, get medical help or contact a Poison Control Center right away

Directions

- change wet and soiled diapers promptly, cleanse the diaper area and allow to dry
- apply ointment liberally as often as necessary, with each diaper change especially at bedtime or anytime when exposure to wet diapers may be prolonged

Other information

- store at 20o to 25oC (68o to 77oF)
- Lot No. and Exp. Date: see box or see crimp of tube

Inactive ingredients

BHA, cod liver oil (high in vitamins A and D), fragrance, lanolin, light mineral oil, methylparaben, petrolatum, purified water, talc, tartrazine yellow #4 (FD and C yellow #4)

DOSAGE AND ADMINISTRATION

Proudly Distributed By:

Western Family Foods, Inc.

P.O. Box 4057, Portland, OR 97208 U.S.A.

Copyright 2010 Marca Registrada

www.westernfamily.com

PACKAGE LABEL

Enter section text here